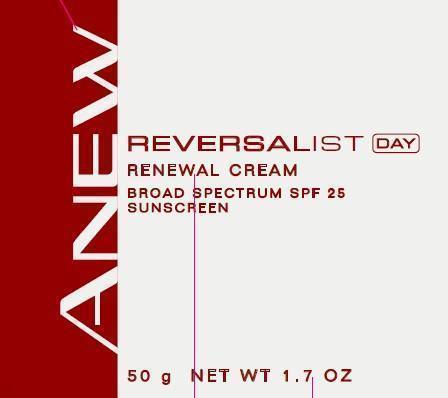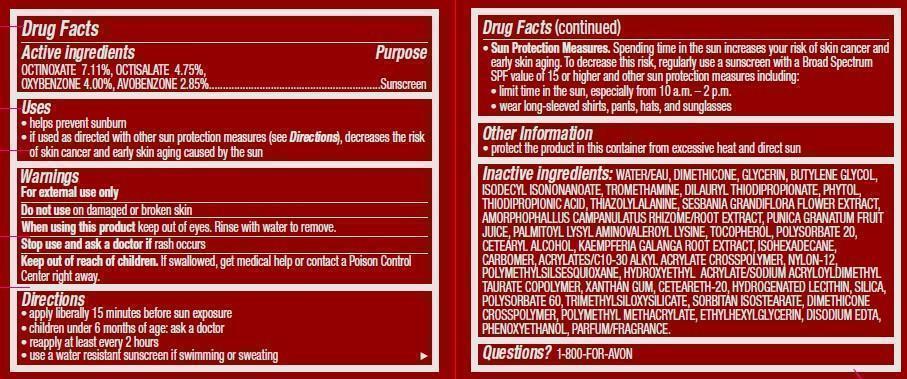 DRUG LABEL: Anew Reversalist
NDC: 10096-0181 | Form: CREAM
Manufacturer: Avon Products, Inc
Category: otc | Type: HUMAN OTC DRUG LABEL
Date: 20130204

ACTIVE INGREDIENTS: OCTINOXATE 71.1 mg/1 g; OCTISALATE 47.5 mg/1 g; OXYBENZONE 40.0 mg/1 g; AVOBENZONE 28.5 mg/1 g

Active ingredients
OCTINOXATE 7.11%, OCTISALATE 4.75%,
OXYBENZONE 4.00%, AVOBENZONE 2.85%.............................................................

Purpose
.....................................Sunscreen

INDICATIONS AND USAGE

Uses• helps prevent sunburn

• if used as directed with other sun protection measures (see Directions), decreases the risk
of skin cancer and early skin aging caused by the sun

Warnings

For external use only

Do not use on damaged or broken skin

When using this product keep out of eyes. Rinse with water to remove.

Stop use and ask a doctor if rash occurs

Keep out of reach of children. If swallowed, get medical help or contact a Poison Control Center right away.

Directions

• apply liberally 15 minutes before sun exposure
• children under 6 months of age: ask a doctor
• reapply at least every 2 hours
• use a water resistant sunscreen if swimming or sweating

• Sun Protection Measures. Spending time in the sun increases your risk of skin cancer and
early skin aging. To decrease this risk, regularly use a sunscreen with a Broad Spectrum
SPF value of 15 or higher and other sun protection measures including:
• limit time in the sun, especially from 10 a.m. – 2 p.m.
• wear long-sleeved shirts, pants, hats, and sunglasses

Other information
• protect the product in this container from excessive heat and direct sun

INACTIVE INGREDIENT

Inactive ingredients: WATER/EAU, DIMETHICONE, GLYCERIN, BUTYLENE GLYCOL,
ISODECYL ISONONANOATE, TROMETHAMINE, DILAURYL THIODIPROPIONATE, PHYTOL,
THIODIPROPIONIC ACID, THIAZOLYLALANINE, SESBANIA GRANDIFLORA FLOWER EXTRACT,
AMORPHOPHALLUS CAMPANULATUS RHIZOME/ROOT EXTRACT, PUNICA GRANATUM FRUIT
JUICE, PALMITOYL LYSYL AMINOVALEROYL LYSINE, TOCOPHEROL, POLYSORBATE 20,
CETEARYL ALCOHOL, KAEMPFERIA GALANGA ROOT EXTRACT, ISOHEXADECANE,
CARBOMER, ACRYLATES/C10-30 ALKYL ACRYLATE CROSSPOLYMER, NYLON-12,
POLYMETHYLSILSESQUIOXANE, HYDROXYETHYL ACRYLATE/SODIUM ACRYLOYLDIMETHYL
TAURATE COPOLYMER, XANTHAN GUM, CETEARETH-20, HYDROGENATED LECITHIN, SILICA,
POLYSORBATE 60, TRIMETHYLSILOXYSILICATE, SORBITAN ISOSTEARATE, DIMETHICONE
CROSSPOLYMER, POLYMETHYL METHACRYLATE, ETHYLHEXYLGLYCERIN, DISODIUM EDTA,
PHENOXYETHANOL, PARFUM/FRAGRANCE.

Questions? Call 1-800-FOR-AVON